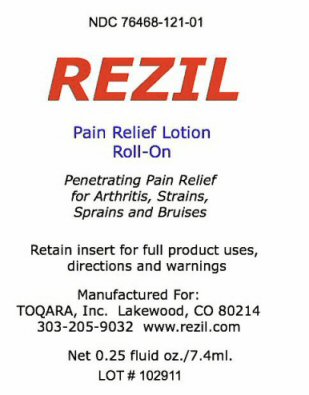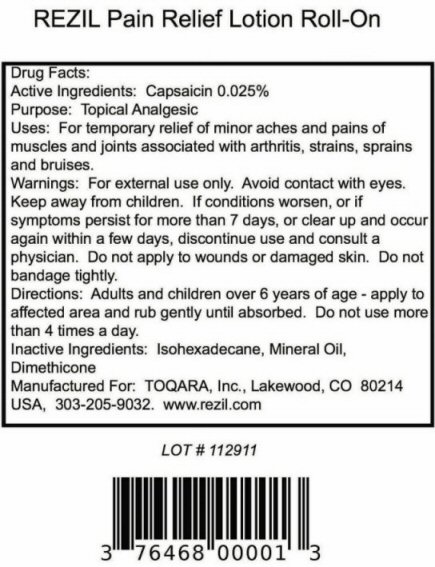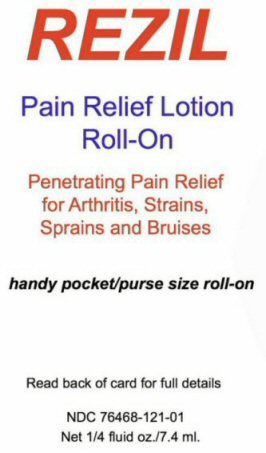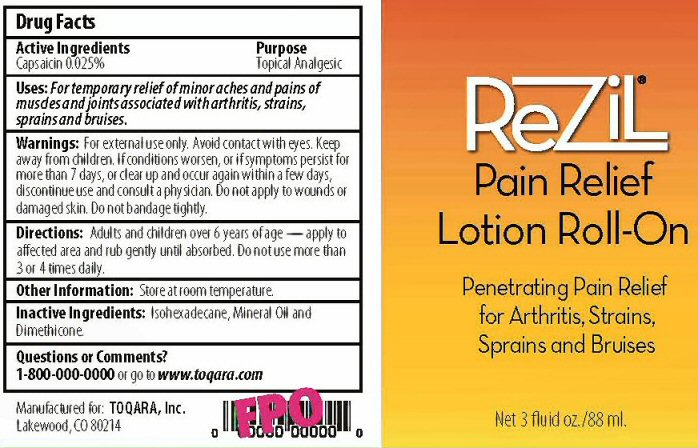 DRUG LABEL: REZIL
NDC: 76468-121 | Form: LOTION
Manufacturer: Toqara, Inc.
Category: otc | Type: HUMAN OTC DRUG LABEL
Date: 20110928

ACTIVE INGREDIENTS: CAPSAICIN 0.025 mL/100 mL
INACTIVE INGREDIENTS: ISOHEXADECANE; MINERAL OIL; DIMETHICONE

ACTIVE INGREDIENTS SECTION

DRUG FACTS

CAPSAICIN 0.025%

PURPOSE SECTION

TOPICAL ANALGESIC

KEEP OUT OF REACH OF CHILDREN SECTION

KEEP AWAY FROM CHILDREN.

INDICATIONS AND USES SECTION

USES: FOR TEMPORARY RELIEF OF MINOR ACHES, AND PAINS OF MUSCLES AND JOINTS ASSOCIATED WITH ARTHRITIS, STRAINS, SPRAINS, AND BRUISES.

WARNINGS SECTION

WARNINGS: FOR EXTERNAL USE ONLY. AVOID CONTACT WITH EYES. IF CONDITION WORSEN, OR IF SYMPTOMS PERSIST FOR MORE THAN 7 DAYS, OR CLEAR UP AND OCCUR AGAIN WITHIN A FEW DAYS, DISCONTINUE USE A CONSULT A PHYSICIAN. DO NOT APPLY TO WOUNDS OR DAMAGED SKIN. DO NOT BANDAGE TIGHTLY.

DOSAGE AND ADMINISTRATION SECTION

DIRECTIONS: ADULTS AND CHILDREN OVER 6 YEARS OF AGE - APPLY TO AFFECTED AREA AND RUB GENTLY UNTIL ABSORBED. DO NOT USE MORE THAN 3 OR 4 TIMES DAILY.

INACTIVE INGREDIENTS SECTION

ISOHEXADECANE, MINERAL OIL AND DIMETHICONE

QUESTIONS OR COMMENTS SECTION

QUESTIONS OR COMMENTS? 1-800-000-0000 OR GO TO WWW.TOQARA.COM

OTHER INFORMATION SECTION

OTHER INFORMATION: STORE AT ROOM TEMPERATURE

PACKAGE LABEL SECTION

REZIL PAIN RELIEF LOTION ROLL-ON

PENETRATING PAIN RELIEF FOR ARTHRITIS, STRAINS, SPRAINS AND BRUISES

NET 3 FLUID OZ./88ML MANUFACTURED FOR TOQARA, INC. LAKEWOOD, CO 80214

REZIL PAIN RELIEF LOTION ROLL-ON PENETRATING PAIN RELIEF FOR ARTHRITIS, STRAINS, SPRAINS AND BRUISES
HANDY POCKET/PURSE SIZE ROLL-ON READ BACK OF CARD FOR FULL DETAILS RETAIN INSERT FOR FULL PRODUCT USES, DIRECTIONS AND WARNINGS
NET 1/4 FLUID OX./7.4 ML.
MANUFACTURED FOR:TOQARA, INC. LAKEWOOD, CO 80214 USA, 303-205-9032 WWW.REZIL.COM